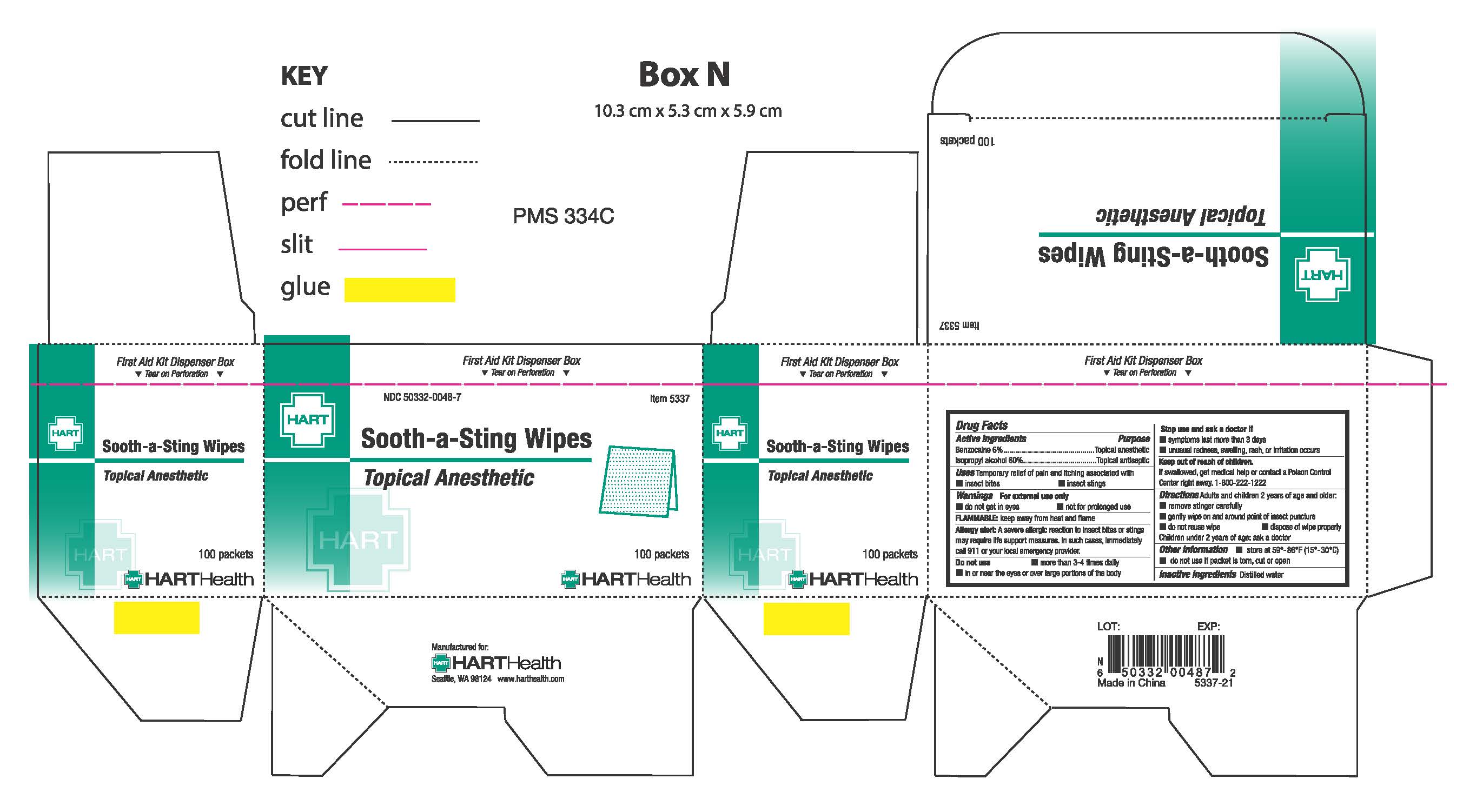 DRUG LABEL: Sooth-a-Sting
NDC: 50332-0048 | Form: SWAB
Manufacturer: HART Health
Category: otc | Type: HUMAN OTC DRUG LABEL
Date: 20260112

ACTIVE INGREDIENTS: BENZOCAINE .06 g/1 g; ISOPROPYL ALCOHOL .60 g/1 g
INACTIVE INGREDIENTS: WATER

SOOTH-A-STING WIPES

Active Ingredients

Benzocaine 6%

Isopropyl Alcohol 60%

Purpose

Topical Anesthetic

Topical Antiseptic

Uses

Temporarily relief of pain and itching associated with

- insect bites
- insect stings

Warnings

For external use only

do not get in eyes

not for prolonged use

FLAMMABLE keep away from heat and flame

Allergy alert: A severe allertic reaction to insect bites and stings may require life support measures. In such cases, immediately call 911 or your local emergency provider.

Do not use

- more than 3 to 4 times daily
- in or near the eyes or over large portions of the body

Stop use and ask a doctor if

- symptoms last more than 3 days
- unusual redness, swelling, rash, or other irriation occurs

Keep out of reach of children

If swallowed, get medical help or contact a Poison Control Center right away 1-800-222-1222

Directions

Adults and chldren 2 years of age and older:

- remover stinger carefully
- gently wipe on and around point of insect puncture
- do not reuse wipe
- dispose of wipe properly

Children under 2 years of age:

- ask a doctor

Inactive Ingredient

Water